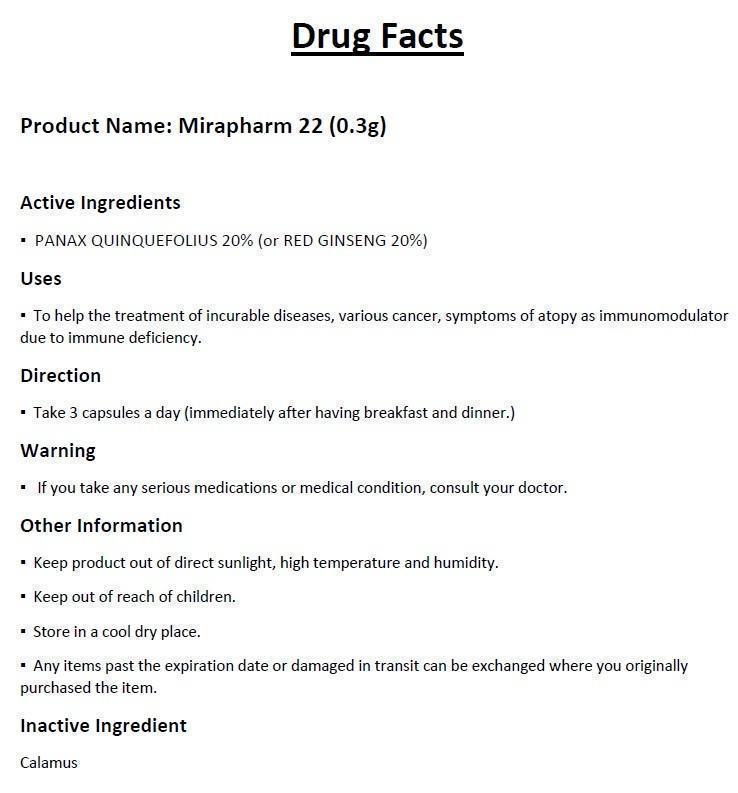 DRUG LABEL: MIRAPHARM 22
NDC: 61065-2001 | Form: CAPSULE
Manufacturer: MIRAPHARM., Inc.
Category: otc | Type: HUMAN OTC DRUG LABEL
Date: 20230518

ACTIVE INGREDIENTS: PANAX QUINQUEFOLIUS WHOLE 0.06 g/1 1
INACTIVE INGREDIENTS: ACORUS CALAMUS ROOT

MIRAPHARM 22

Active ingredients

- PANAX QUINQUEFOLIUS 20% (or RED GINSENG 20%)

Purpose

Stimulant

Keep out of reach of children.

Uses

- To help the treatment of incurable diseases, various cancer, symptoms of atopy as immunomodulator due to immune deficiency.

Warning

- If you take any serious medications or medical condition, consult your doctor

Direction

- Take 3 capsules a day (immediately after having breakfast and dinner.)

Other Information

- Keep product out of direct sunlight, high temperature and humidity.
- Store in a cool dry place.
- Any items past the expiration date or damaged in transit can be exchanged where you originally purchased the item.

Inactive Ingredient

Calamus